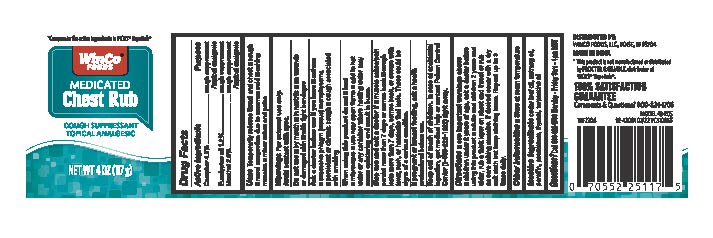 DRUG LABEL: Winco Foods Medicated Chest Rub
NDC: 67091-410 | Form: OINTMENT
Manufacturer: WinCo Foods, LLC
Category: otc | Type: HUMAN OTC DRUG LABEL
Date: 20251228

ACTIVE INGREDIENTS: CAMPHOR (SYNTHETIC) 0.048 g/1 g; EUCALYPTUS OIL 0.012 g/1 g; MENTHOL 0.026 g/1 g
INACTIVE INGREDIENTS: NUTMEG OIL; THYMOL; TURPENTINE OIL; PETROLATUM; PARAFFIN; CEDAR LEAF OIL

WinCo Foods Medicated Chest Rub

Drug Facts

ACTIVE INGREDIENT

Camphor (synthetic) 4.8%
Eucalyptus oil 1.2%
Menthol 2.6%

PURPOSE

Cough suppressant & topical analgesic
Cough suppressant
Cough suppressant & topical analgesic

Uses

Temporarily relieves throat and chest

- cough
- aching muscles
- minor aches and pains

Warnings

For external use only; avoid contact with eyes.

Do not use

- by mouth
- in nostrils
- on wounds or damaged skin
- with tight bandages

Ask a doctor before use if you have

- asthma
- excessive phlegm (mucus)
- emphysema
- persistent or chronic cough
- cough associated with smoking

When using this product, do not

- heat
- microwave
- use near open flame
- add to hot water or any container where heating water may cause splattering and result in burns
  .

Stop use and ask a doctor if

- muscle aches and pain persist for more than 7 days or comes back.
- cough lasts more than 7 days, comes back, or occurs with fever, rash, or headache that lasts. These could be signs of a seriuos condition

PREGNANCY OR BREAST FEEDING

If pregnant or breast-feeding, ask a health professional before use.

Keep out of reach of children. In case of accidental ingestion, get medical help or contact a Poison Control Center (1-800-222-1222) right away.

Directions

see important warnings above

- children under 2 years of age, ask a doctor before using this product
- adults and children 2 years and older, rub a thick layer on chest and throat or rub on sore aching muscles If desired cover with a dry soft cloth but keep clothing loose. Repeat up to 3 times daily

Other information

- store at room temperature

Inactive ingredients

cedar leaf oil, nutmeg oil, paraffin, petrolatum, thymol, turpentine oil

Questions?

800-824-1706 Monday-Friday 9am-4pm MST